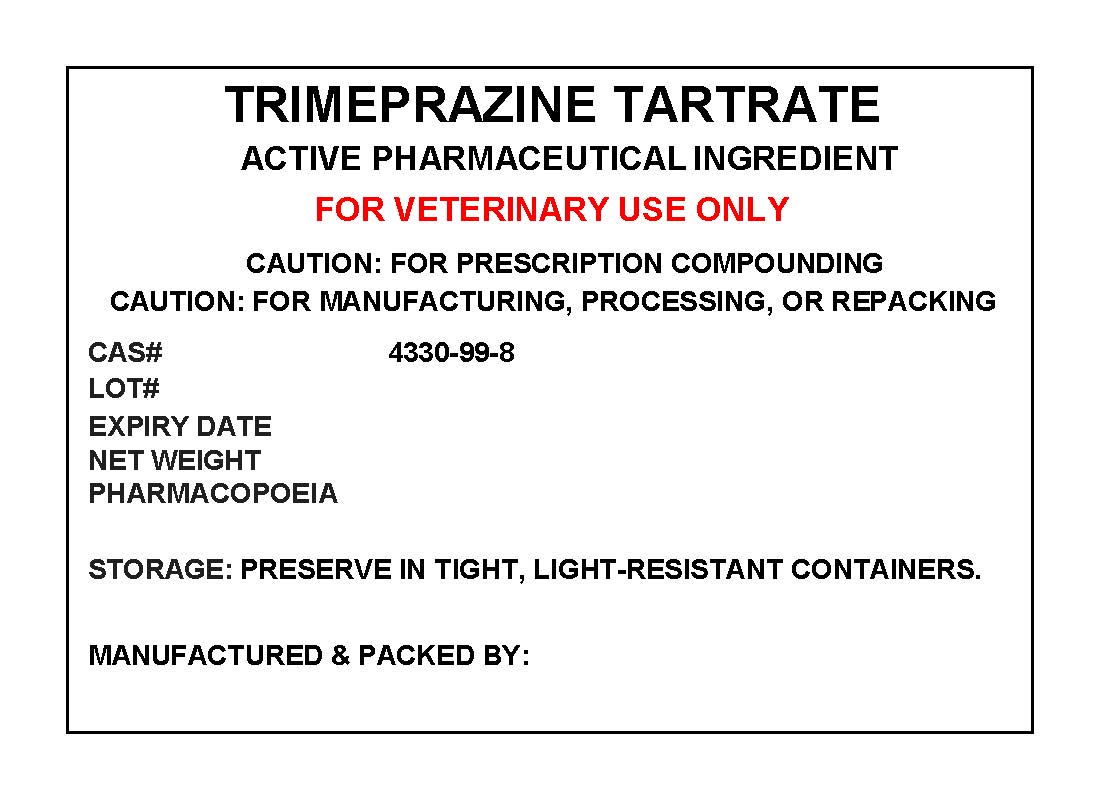 DRUG LABEL: TRIMEPRAZINE TARTRATE
NDC: 72969-075 | Form: POWDER
Manufacturer: PROFESSIONAL GROUP OF PHARMACISTS NEW YORK LLC
Category: other | Type: BULK INGREDIENT
Date: 20190314

ACTIVE INGREDIENTS: TRIMEPRAZINE TARTRATE 1 g/1 g

TRIMEPRAZINE TARTRATE

PACKAGE LABEL

trimeprazinelabel.jpg